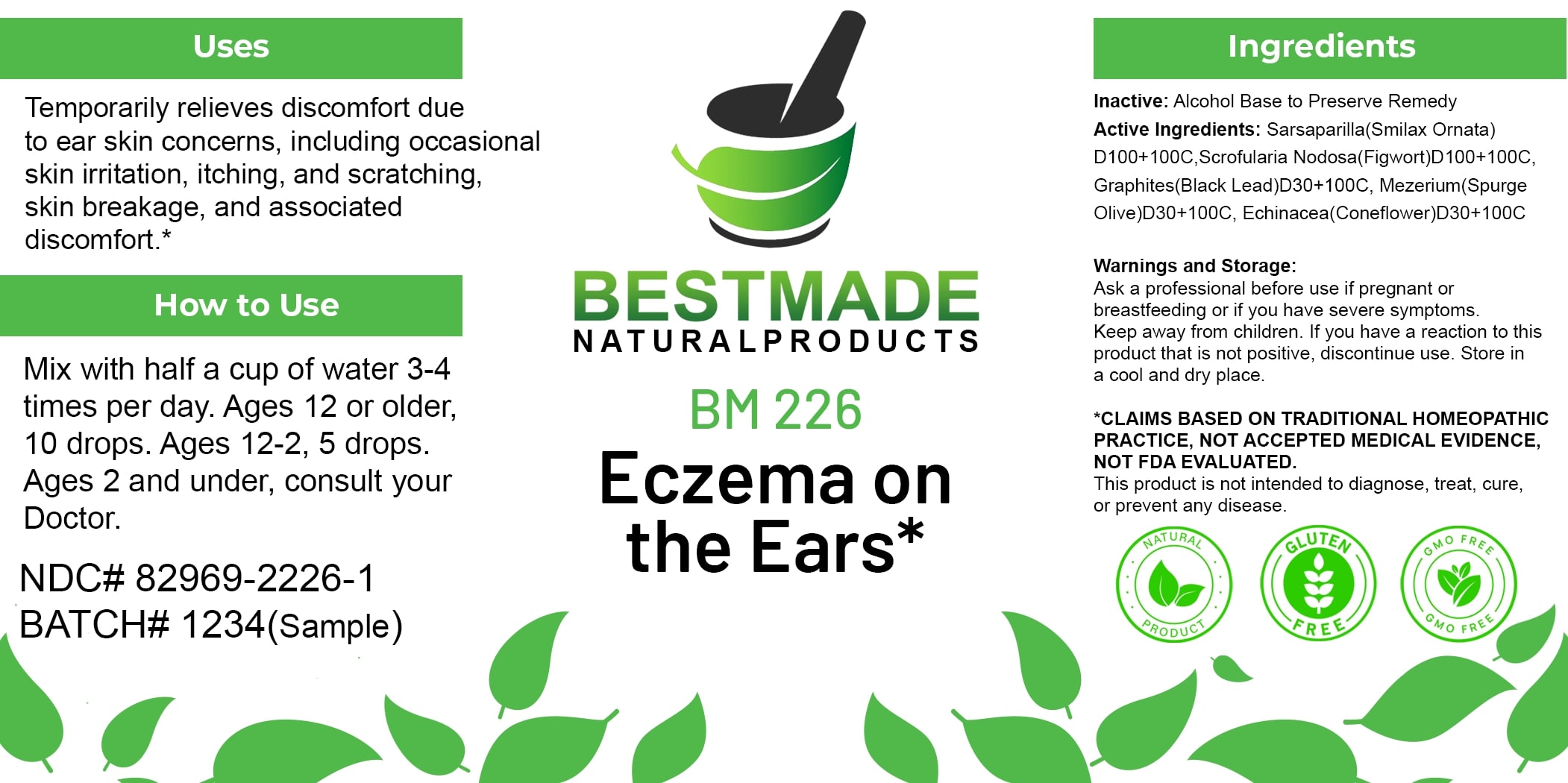 DRUG LABEL: Bestmade Natural Products BM226
NDC: 82969-2226 | Form: LIQUID
Manufacturer: Bestmade Natural Products
Category: homeopathic | Type: HUMAN OTC DRUG LABEL
Date: 20250303

ACTIVE INGREDIENTS: ECHINACEA, UNSPECIFIED 100 [hp_C]/100 [hp_C]; DAPHNE MEZEREUM BARK 100 [hp_C]/100 [hp_C]; SCROPHULARIA NODOSA 100 [hp_C]/100 [hp_C]; GRAPHITE 100 [hp_C]/100 [hp_C]; SARSAPARILLA 100 [hp_C]/100 [hp_C]
INACTIVE INGREDIENTS: ALCOHOL 100 [hp_C]/100 [hp_C]

BM226

DOSAGE AND ADMINISTRATION

How to Use

Mix with half a cup of water 3-4 times per day. Ages 12 or older, 10 drops. Ages 12-2, 5 drops. Ages 2 and under, consult your Doctor.

Uses

Temporarily relieves discomfort due to ear skin concerns, including occasional skin irritation, itching, and scratching, skin breakage, and associated discomfort.*

*CLAIMS BASED ON TRADITIONAL HOMEOPATHIC PRACTICE, NOT ACCEPTED MEDICAL EVIDENCE. NOT FDA EVALUATED.

This product is not intended to diagnose, treat, cure, or prevent any disease.

ACTIVE INGREDIENT

Active Ingredients: Sarsaparilla(Smilax Ornata) D100+100C, Scrofularia Nodosa(Figwort)D100+100C, Graphites(Black Lead)D30+100C, Mezereum(Spurge Olive)D30+100C, Echinacea(Coneflower)D30+100C

INACTIVE INGREDIENT

Ingredients

Inactive: Alcohol Base to Preserve Remedy

KEEP OUT OF REACH OF CHILDREN

Warnings and Storage:

Ask a professional before use if pregnant or breastfeeding or if you have severe symptoms. Keep away from children. If you have a reaction to this product that is not positive, discontinue use. Store in a cool and dry place.

Warnings and Storage:

Ask a professional before use if pregnant or breastfeeding or if you have severe symptoms. Keep away from children. If you have a reaction to this product that is not positive, discontinue use. Store in a cool and dry place.

*CLAIMS BASED ON TRADITIONAL HOMEOPATHIC PRACTICE, NOT ACCEPTED MEDICAL EVIDENCE. NOT FDA EVALUATED.

This product is not intended to diagnose, treat, cure, or prevent any disease.

Uses

Temporarily relieves discomfort due to ear skin concerns, including occasional skin irritation, itching, and scratching, skin breakage, and associated discomfort.*

*CLAIMS BASED ON TRADITIONAL HOMEOPATHIC PRACTICE, NOT ACCEPTED MEDICAL EVIDENCE. NOT FDA EVALUATED.

This product is not intended to diagnose, treat, cure, or prevent any disease.

Entire package label